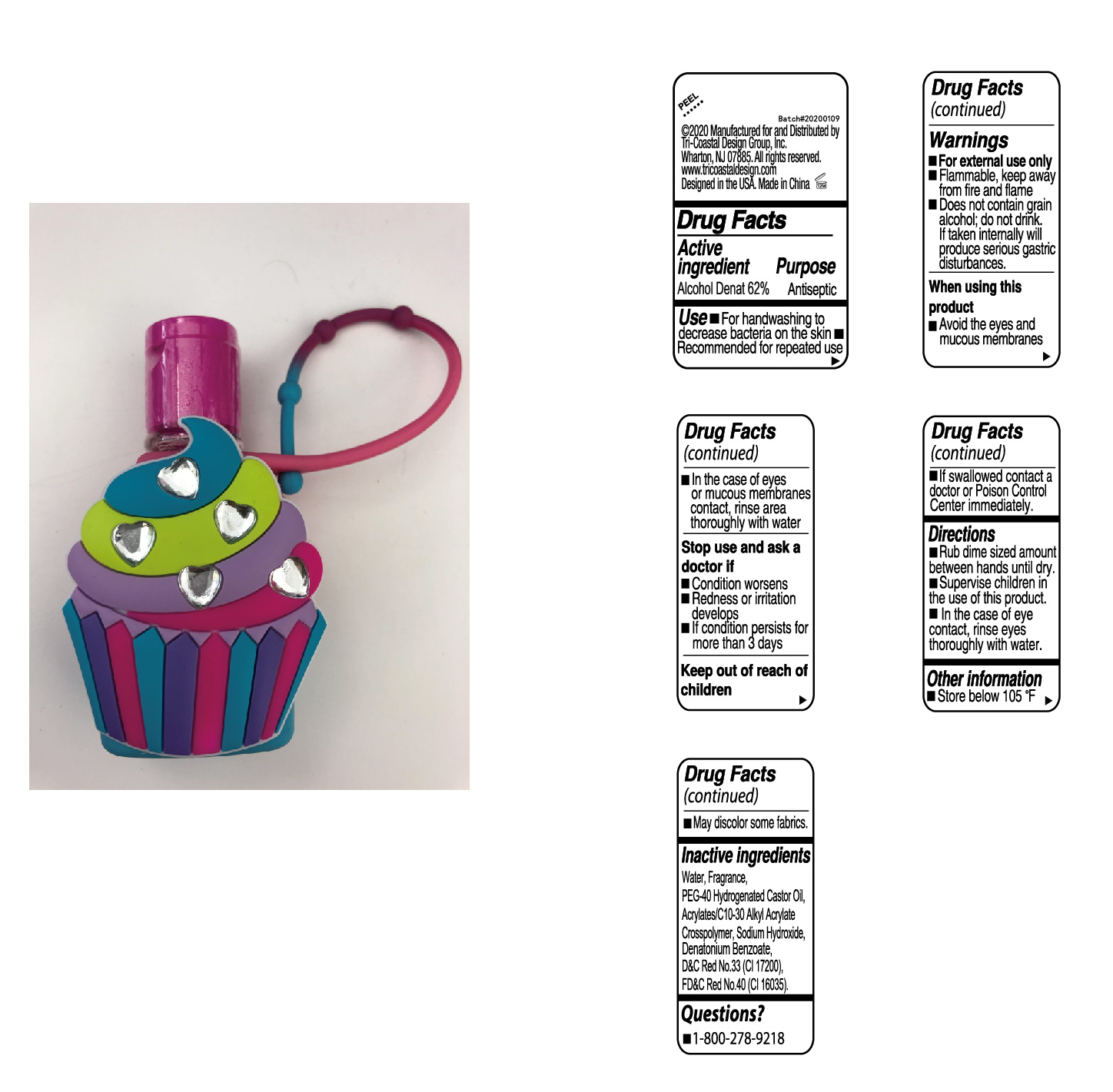 DRUG LABEL: Hand Sanitizer
NDC: 76383-088 | Form: GEL
Manufacturer: BBC Group Limited
Category: otc | Type: HUMAN OTC DRUG LABEL
Date: 20200703

ACTIVE INGREDIENTS: ALCOHOL 62 g/100 mL
INACTIVE INGREDIENTS: FD&C RED NO. 40; D&C RED NO. 33; POLYOXYL 40 HYDROGENATED CASTOR OIL; CARBOMER INTERPOLYMER TYPE A (55000 CPS); WATER; SODIUM HYDROXIDE; DENATONIUM BENZOATE

BBC TriCstl Hand Santizer 62 Brght Pink

Active ingredient

Alcohol Denat 62%

Purpose

Antiseptic

Use

■ For handwashing to decrease bacteria on the skin ■ Recommended for repeated use

Warnings

■ For external use only

■ Flammable, keep away from fire & flame

■ Does not contain grain alcohol;do not drink. If taken internally will produce serious gastric disturbances.

When using this product

■ Avoid the eyes and mucous membranes ■ In the case of eyes or mucous membrane contact, rinse area thoroughly with water

Stop use and ask a doctor if

■ Condition worsens

■ Redness or irritation develops

■ If condition persists for more than 3 days

Keep out of reach of children

■ If swallowed contact a doctor or Poison Control Center immediately.

Directions

■ Rub dime sized amount between hands until dry

■ Supervise children in the use of this product

■ In the case of eye contact, rinse eyes thoroughly with water

Other information

■ Store below 105°F

■ May discolor some fabrics

Inactive Ingredients

Water, Fragrance, PEG-40 Hydrogenated Castor Oil, Acrylates/C10-30 Alkyl Acrylate Crosspolymer, Sodium Hydroxide, Denatonium Benzoate, D&C Red No. 33(CI 17200), FD&C Red No. 40(CI 16035)

Questions?

■ 1-800-278-9218